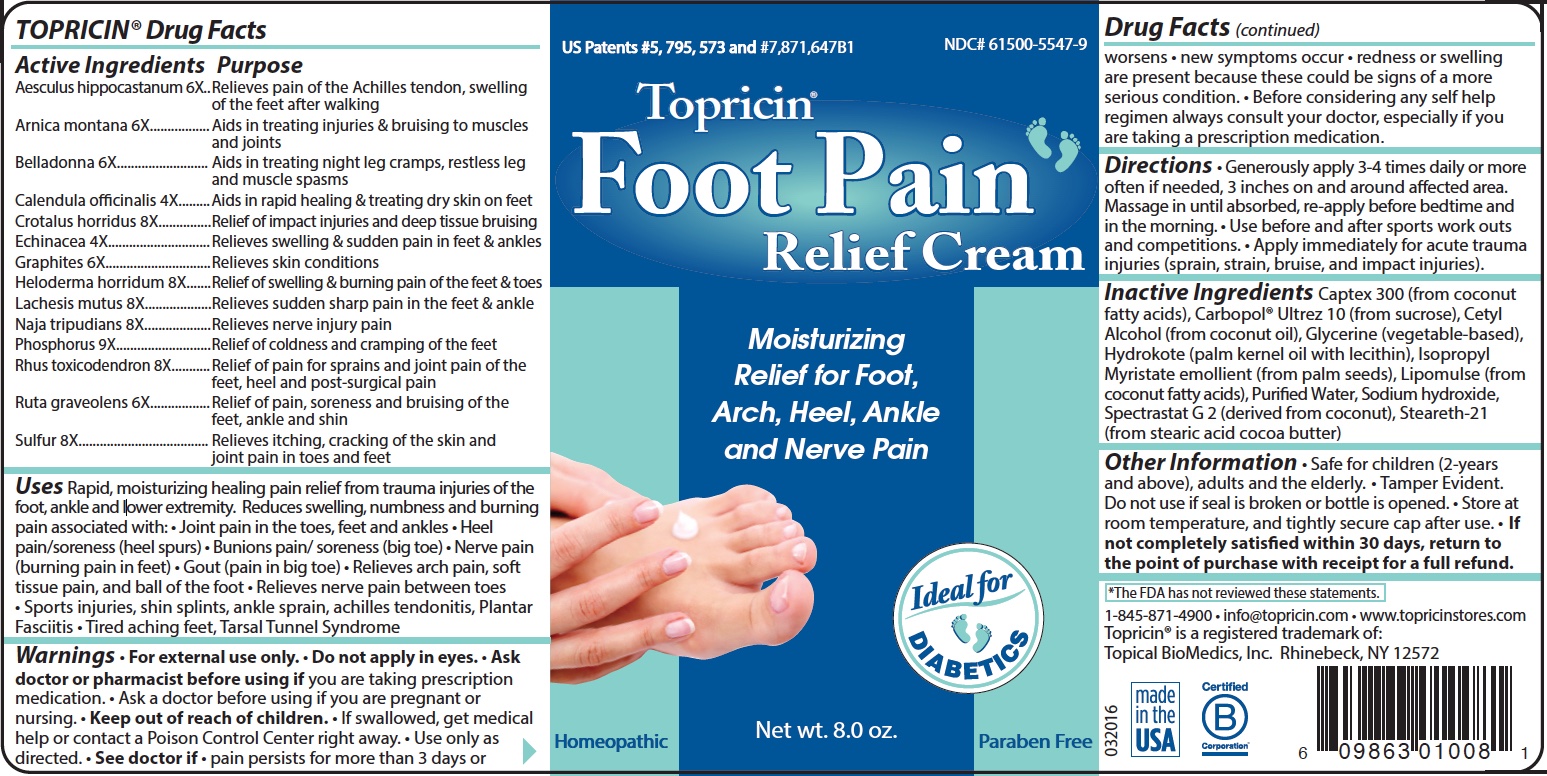 DRUG LABEL: Topricin
NDC: 61500-5547 | Form: CREAM
Manufacturer: Topical BioMedics, Inc.
Category: homeopathic | Type: HUMAN OTC DRUG LABEL
Date: 20251003

ACTIVE INGREDIENTS: PHOSPHORUS 9 [hp_X]/227 g; ARNICA MONTANA 6 [hp_X]/227 g; CROTALUS HORRIDUS HORRIDUS VENOM 8 [hp_X]/227 g; ECHINACEA ANGUSTIFOLIA 4 [hp_X]/227 g; GRAPHITE 6 [hp_X]/227 g; HELODERMA HORRIDUM VENOM 8 [hp_X]/227 g; LACHESIS MUTA VENOM 8 [hp_X]/227 g; NAJA NAJA VENOM 8 [hp_X]/227 g; RUTA GRAVEOLENS FLOWERING TOP 6 [hp_X]/227 g; AESCULUS HIPPOCASTANUM FLOWER 6 [hp_X]/227 g; ATROPA BELLADONNA 6 [hp_X]/227 g; TOXICODENDRON PUBESCENS LEAF 8 [hp_X]/227 g; CALENDULA OFFICINALIS FLOWERING TOP 4 [hp_X]/227 g; SULFUR 8 [hp_X]/227 g
INACTIVE INGREDIENTS: CAPRYLHYDROXAMIC ACID; CAPRYLIC/CAPRIC TRIGLYCERIDE; GLYCERIN; WATER; STEARETH-20; GLYCERYL MONOSTEARATE; HYDROGENATED PALM KERNEL OIL; CETYL ALCOHOL; CARBOMER INTERPOLYMER TYPE A (ALLYL SUCROSE CROSSLINKED); SODIUM HYDROXIDE; GLYCERYL CAPRYLATE; ISOPROPYL MYRISTATE

Topricin Foot Therapy Cream [2g, 0.75oz, 2oz, 4oz, 8oz, 16 oz]

Active Ingredients

Aesculus hippocastanum 6X

Arnica montana 6X

Belladona 6X

Calendula officinalis 4X

Crotalus horridus 8X

Echinacea 4X

Graphites 6X

Heloderma horridum 8X

Lachesis mutus 8X

Naja tripudians 8X

Phosphorus 9X

Rhus toxicodendron 8X

Ruta graveolens 6X

Sulfur 8X

Uses

Rapid, moisturizing healing pain relief from trauma injuries of the foot, ankle and lower extremity.

Reduces swelling, numbness and burning pain associated with:

Joint pain in the toes, feet and ankles

Heel pain/soreness (heel spurs)

Bunions pain/soreness (big toe)

Nerve pain (burning pain in feet)

Gout (pain in big toe)

Relieves arch pain, soft tissue pain, and ball of the foot

Relieves nerve pain between toes

Sports injuries, shin splints, ankle sprain, Achilles tendonitis, Plantar Fasciitis

Tired aching feet, Tarsal Tunnel Syndrome

Purpose

Relieves pain of the Achilles tendon, swelling of the feet after walking

Aids in treating injuries & bruising to muscles and joints

Aids in treating night leg cramps, restless leg and muscle spasms

Aids in rapid healing & treating dry skin on feet

Relief of impact injuries & sudden pain in feet & ankles

Relieves skin conditions

Relief of swelling & burning pain o the feet & toes

Relieves sudden sharp pain in the feet & ankle

Relieves nerve injury pain

Relief of coldness and cramping of the feet

Relief of pain for sprains and joint pain of the feet, heel and post-surgical pain

Relief of pain, soreness and bruising of the feet, ankle and shin

Relieves itching, cracking of the skin and joint pain in toes and feet

Warnings

For external use only. Do not apply in eyes. Ask doctor or pharmacist before using ifyou are taking prescription medication. Ask a doctor before using if you are pregnant or nursing. Keep out of reach of children.If swallowed, get medical help or contact a Poison Control Center right away. Use only as directed. See doctor ifpain persists for more than 3 days or worsens, new symptoms occur, redness or swelling are present because these could be signs of a more serious condition. Before considering any self help regimen always consult your doctor, especially if you are taking a prescription medication.

Directions

Generously apply 3-4 times daily or more often if needed, 3 inches on and around affected area. Massage in until absorbed, re-apply before bedtime and in the morning.

Use before and after sports work outs and competitions.

Apply immediately for acute trauma injuries (sprain, strain, bruise, and impact injuries).

Inactive Ingredients

Captex 300 (from coconut fatty acids), Carbopol® Ultrez 10 (from sucrose), Cetyl Alcohol (from coconut oil), Glycerine (vegetable-based), Hydrokote (palm kernel oil with lecithin), Isopropyl Myristate emollient (from palm seeds), Lipomulse (from coconut fatty acids), Purified Water, Sodium hydroxide, Spectrastat G 2 (derived from coconut), Steareth-21 (from stearic acid cocoa butter)

Other Information

Safe for children (2-years and above), adults and the elderly. Tamper Evident. Do not use if seal is broken or bottle is opened. Store at room temperature, and tightly secure cap after use. No odor or fragrance, no petroleum, no mineral oil, no lanolin, no capsaicin, no menthol, non-greasy, non-staining. If not completely satisfied within 30 days, return to the point of purchase with receipt for a full refund.For severe injury, always seek medical attention.

Principal Display Panel

US Patents # 5,795,573 and #7,871,647

NDC# 61500-5547

Topricin®

Foot Pain Relief Cream

Moisturizing Relief for Foot, Arch, Hell, Ankle and Nerve Pain

Ideal for Diabetics

Homepathic

Net wt. 8.0 oz.

Paraben Free